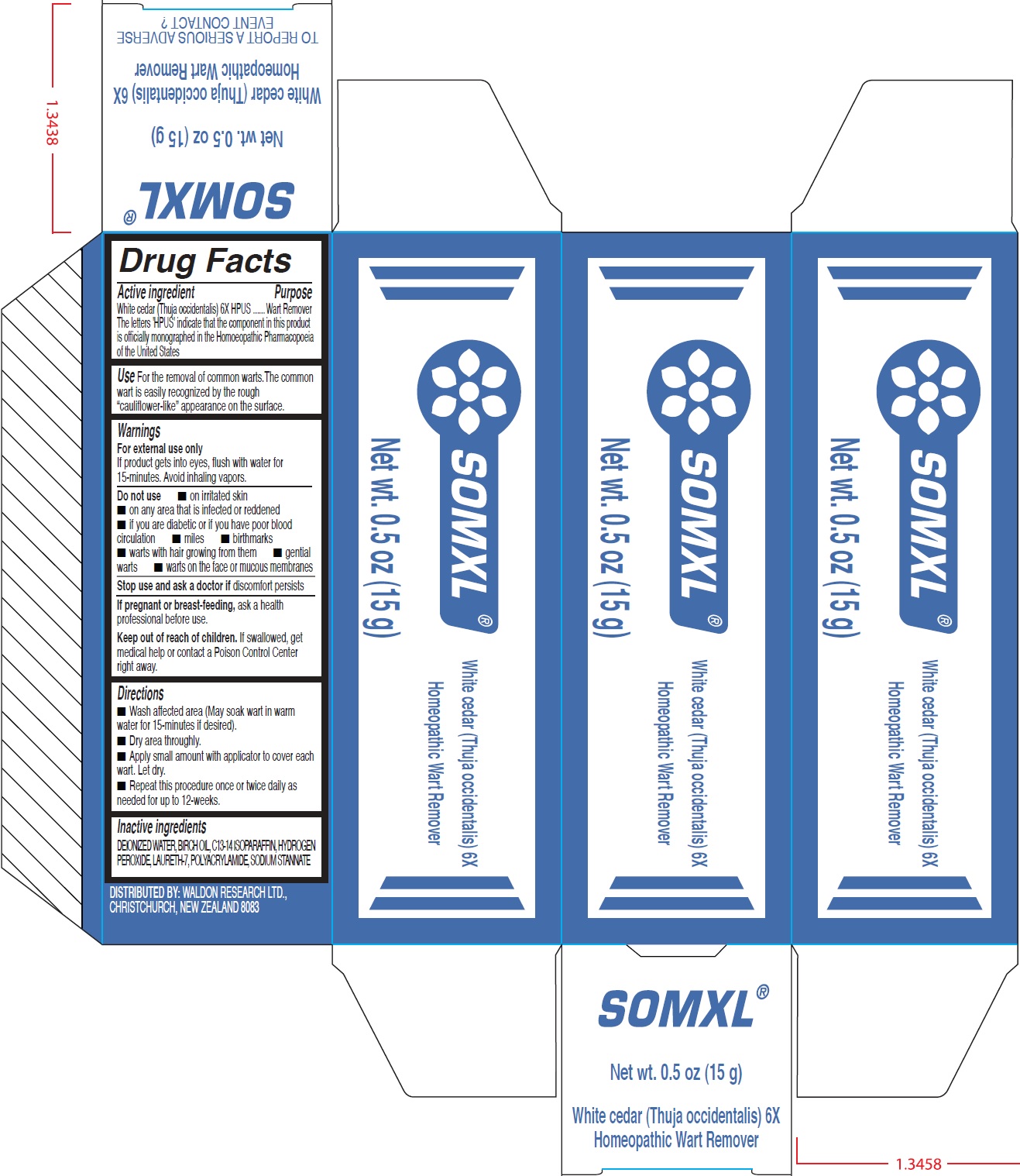 DRUG LABEL: SOMXL Homeopathic Wart Remover
NDC: 70463-725 | Form: CREAM
Manufacturer: WR Group Skin Care Ltd
Category: homeopathic | Type: HUMAN OTC DRUG LABEL
Date: 20250303

ACTIVE INGREDIENTS: THUJA OCCIDENTALIS LEAFY TWIG 6 [hp_X]/15 g
INACTIVE INGREDIENTS: WATER; C13-14 ISOPARAFFIN; HYDROGEN PEROXIDE; LAURETH-7; SODIUM STANNATE

SOMXL Homeopathic Wart Remover

Active ingredient

White cedar (Thuja occidentalis) 6X HPUS ...... The letters 'HPUS' indicate that the component in this product
is officially monographed in the Homoeopathic Pharmacopoeia of the United States

Purpose

Wart Remover

Use

For the removal of common warts. The common wart is easily recognized by the rough “cauliflower-like” appearance on the surface.

Warnings

For external use only
If product gets into eyes, flush with water for 15-minutes. Avoid inhaling vapors.

Do not use

• on irritated skin • on any area that is infected or reddened • if you are diabetic or if you have poor blood circulation • miles • birthmarks • warts with hair growing from them • gential warts • warts on the face or mucous membranes

Stop use and ask a doctor if

discomfort persists

If pregnant or breast-feeding,

ask a health professional before use.

Keep out of reach of children.

If swallowed, get medical help or contact a Poison Control Center right away.

Directions

•Wash affected area (May soak wart in warm water for 15-minutes if desired). • Dry area throughly. • Apply small amount with applicator to cover each wart. Let dry. • Repeat this procedure once or twice daily as needed for up to 12-weeks.

Inactive ingredients

DEIONIZED WATER, BIRCH OIL, C13-14 ISOPARAFFIN, HYDROGEN PEROXIDE, LAURETH-7, POLYACRYLAMIDE, SODIUM STANNATE